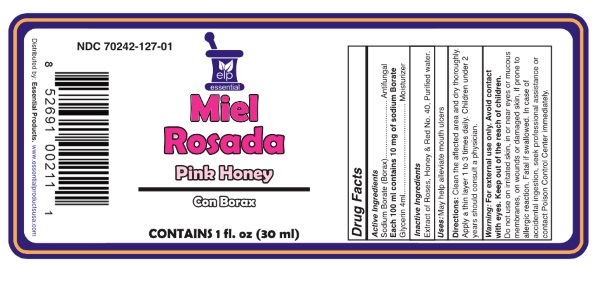 DRUG LABEL: Miel Rosada
NDC: 70242-127 | Form: SOLUTION
Manufacturer: Dannso Corp./d.b.a. Essential Products
Category: otc | Type: HUMAN OTC DRUG LABEL
Date: 20230101

ACTIVE INGREDIENTS: SODIUM BORATE 0.1 mg/1 mL; GLYCERIN 0.4 mg/1 mL
INACTIVE INGREDIENTS: FD&C RED NO. 40; HONEY; WATER

Miel Rosada

Active Ingredients Purpose

SODIUM BORATE .............................. Antifungal

Glycerin ................................................. Moisturizer

Use

May help aliviate mouth ulcers

Keep out of reach of children. If swallowed, get medical help or contact a Poison Control Center right away.

INDICATIONS AND USAGE

Antifuncgal

For External Use Only

Directions

- clean the affected area
- and dry thoroughly. Apply a thin layer 1 to 3 times daily.
- May be covered with a sterile bandage, let dry first.
- Children under 2 years should consult a physician.

Warnings For external use only

Avoid Contact with eyes.

When using this product

- do not use on irritated skin, in or near eyes or mocous membranes, on wounds or damaged skin, if prone to allergic reaction
- Fatal if swallowed.

Stop use and ask a doctor if condition persists or gets worse

INACTIVE INGREDIENT

Inactive Ingredients Extract of Roses, Honey , FD&C red # 40, Purified Water